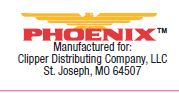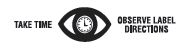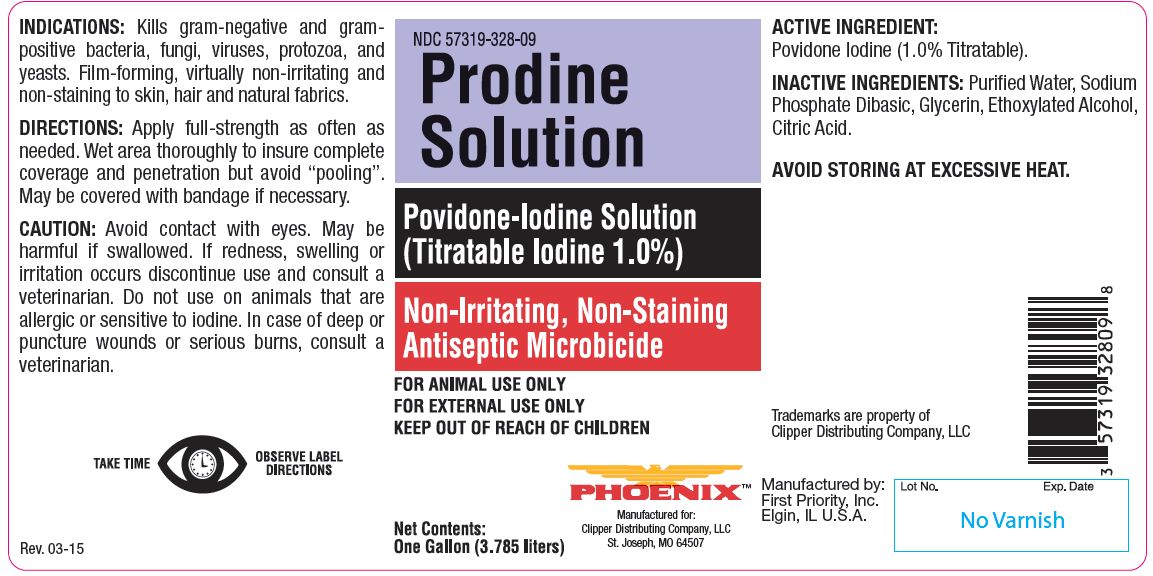 DRUG LABEL: Prodine
NDC: 57319-328 | Form: SOLUTION
Manufacturer: PHOENIX PHARMACEUTICAL INC./ CLIPPER DISTRIBUTING, INC.
Category: animal | Type: OTC ANIMAL DRUG LABEL
Date: 20180123

ACTIVE INGREDIENTS: POVIDONE-IODINE 65.9 g/1 L

Prodine Solution

Povidone-Iodine Solution (Titratable Iodine 1.0%)

Non-Irritating, Non-Staining Antiseptic Microbicide

KEEP OUT OF REACH OF CHILDREN

FOR ANIMAL USE ONLY

FOR EXTERNAL USE ONLY

KEEP OUT OF REACH OF CHILDREN

INDICATIONS:

Kills gram-negative and grampositive bacteria, fungi, viruses, protozoa, and yeasts. Film-forming, virtually non-irritating and non-staining to skin, hair and natural fabrics.

DIRECTIONS:

Apply full-strength as often as needed. Wet area thoroughly to insure complete coverage and penetration but avoid “pooling”. May be covered with bandage if necessary.

CAUTION:

Avoid contact with eyes. May be harmful if swallowed. If redness, swelling or irritation occurs discontinue use and consult a veterinarian. Do not use on animals that are allergic or sensitive to iodine. In case of deep or puncture wounds or serious burns, consult a veterinarian.

ACTIVE INGREDIENT:

Povidone Iodine (1.0% Titratable).

INACTIVE INGREDIENTS:

Purified Water, Sodium Phosphate Dibasic, Glycerin, Ethoxylated Alcohol, Citric Acid.

STORAGE AND HANDLING

AVOID STORING AT EXCESSIVE HEAT.

Net Contents

One Gallon (3.785 liters)

INFORMATION FOR OWNERS/CAREGIVERS

Trademarks are property of Clipper Distributing Company, LLC

Manufactured by:
First Priority, Inc.
Elgin, IL U.S.A.